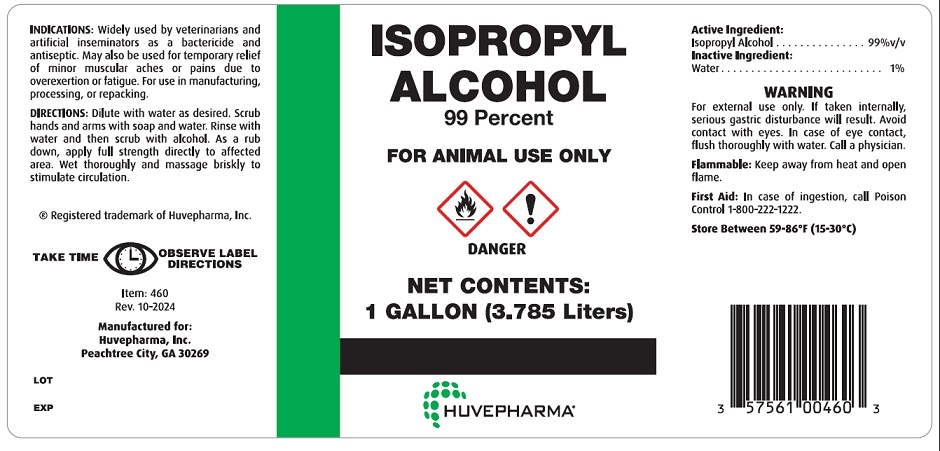 DRUG LABEL: ISOPROPYL ALCOHOL
NDC: 23243-0338 | Form: LIQUID
Manufacturer: Huvepharma, Inc
Category: animal | Type: OTC ANIMAL DRUG LABEL
Date: 20250701

ACTIVE INGREDIENTS: ISOPROPYL ALCOHOL 99 L/100 L
INACTIVE INGREDIENTS: WATER 1 L/100 L

INDICATIONS AND USAGE

ISOPROPYL ALCOHOL

99 Percent

FOR ANIMAL USE ONLY

Active Ingredients:

Isopropyl Alcohol ................. 99% v/v

Inactive Ingredients:

Water .................................1%

INDICATIONS: Widely used by veterinarians and artificial inseminators as a bactericide and antiseptic. May also be used for temporary relief of minor muscular aches or pains due to overexertion or fatigue. For use in manufacturing, processing, or repacking.

DIRECTIONS: Dilute with water as desired. Scrub hands and arms with soap and water. Rinse with water and then scrub with alcohol. As a rubdown, apply full strength directly to affected area. Wet thoroughly and massage briskly to stimulate circulation.

WARNING: For external use only. If taken internally, serious gastric disturbance will result. Avoid contact with eyes. In case of eye contact, flush thoroughly with water. Call a physician.

Flammable: Keep away from heat or open flames.

First Aid: In case of ingestion, call Poison Control 1-800-222-1222.

Store Between 59-86°F (15-30°C)

Manufactured for:

Huvepharma, Inc.

Peachtree City, GA 30269